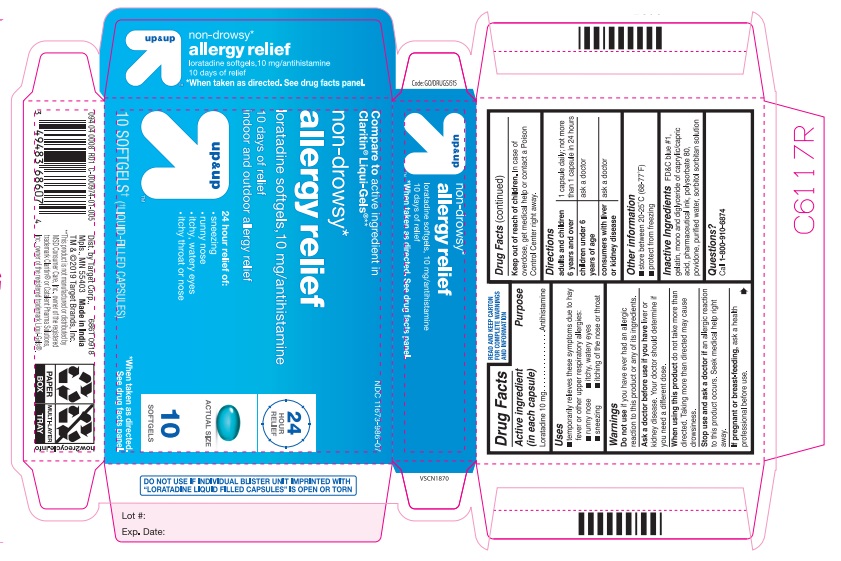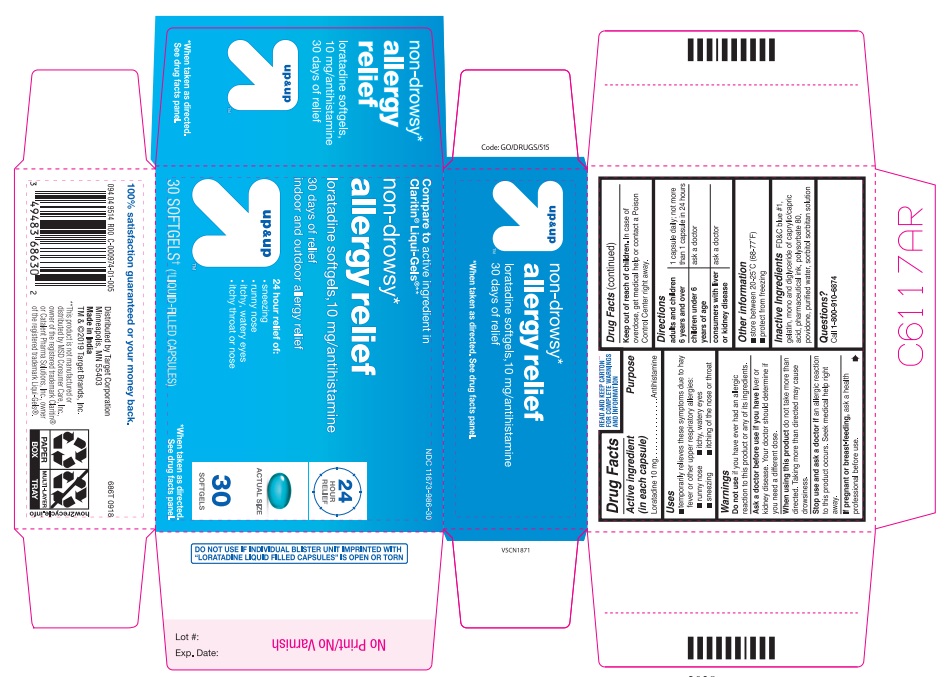 DRUG LABEL: ALLERGY RELIEF
NDC: 11673-986 | Form: CAPSULE, LIQUID FILLED
Manufacturer: TARGET CORPORATION
Category: otc | Type: HUMAN OTC DRUG LABEL
Date: 20250201

ACTIVE INGREDIENTS: LORATADINE 10 mg/1 1
INACTIVE INGREDIENTS: POVIDONE; GLYCERYL MONO- AND DICAPRYLOCAPRATE; FD&C BLUE NO. 1; GELATIN; SORBITOL; WATER; POLYSORBATE 80

TARGET 686T LORATADINE 10 MG SOFT GELS TARGET NDC 11673-986-07 (10CT)11673-986-30 (30ct)

Active ingredient (in each capsule)

Loratadine 10 mg

Purpose

Antihistamine

INDICATIONS AND USAGE

TEMPORARILY RELIEVES THESE SYMPTOMS DUE TO HAY FEVER OR OTHR UPPER RESPIRATORY ALLERGIES:

RUNNY NOSE

ITCHY, WATERY EYES

SNEEZING

ITCHING OF THE NOSE OR THROAT

Warnings

Do not use if you have ever had an allergic reaction to this product or any of its ingredients.

Ask a doctor before use if you have liver or kidney disease. Your doctor should determine if you need a different dose.

When using this product do not take more than directed. Taking more than directed may cause drowsiness.

Stop use and ask a doctor if an allergic reaction to this product occurs, Seek medical help right away.

PREGNANCY OR BREAST FEEDING

If pregnant or breast-feeding, ask a health professional before use.

Keep out of reach of children. In case of overdose, get medical help or contact a Poison Control Center right away (1-800-222-1222).

Directions

adults and children 6 years and over | 1 capsule daily; not more than 1 capsule in 24 hours
children under 6 years of age | ask a doctor
consumers with liver or kidney disease | ask a doctor

Other information

- store between 20-25°C (68-77°F)
- protect from freezing

Inactive ingredients

FD&C blue # 1, gelatin, mono and diglyceride of caprylic/capric acid, pharmaceutical ink, polysorbate 80, povidone, purified water, sorbitol sorbitan solution

Questions or comments?

Call 1-877-290-4008